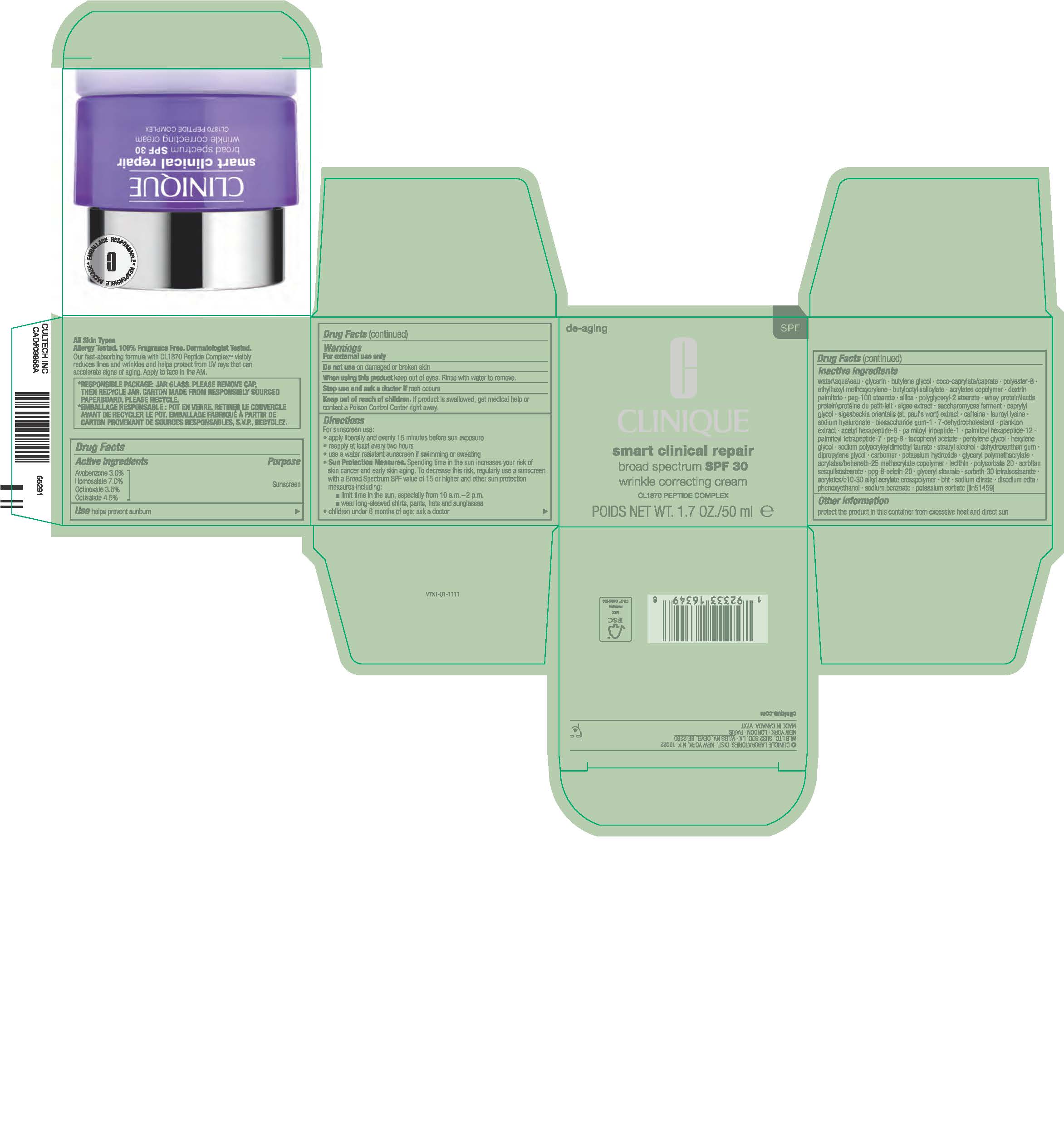 DRUG LABEL: SMART CLINICAL REPAIR BROAD SPECTRUM SPF 30
NDC: 49527-083 | Form: CREAM
Manufacturer: CLINIQUE LABORATORIES LLC
Category: otc | Type: HUMAN OTC DRUG LABEL
Date: 20231115

ACTIVE INGREDIENTS: AVOBENZONE 30 mg/1 mL; HOMOSALATE 70 mg/1 mL; OCTINOXATE 35 mg/1 mL; OCTISALATE 45 mg/1 mL
INACTIVE INGREDIENTS: PEG-100 STEARATE; POLYGLYCERYL-2 STEARATE; WHEY; PORPHYRIDIUM PURPUREUM; CAPRYLYL GLYCOL; HYALURONATE SODIUM; 7-DEHYDROCHOLESTEROL; ACETYL HEXAPEPTIDE-8; GLYCERIN; BUTYL ACRYLATE/METHYL METHACRYLATE/METHACRYLIC ACID COPOLYMER (18000 MW); DEXTRIN PALMITATE (CORN; 20000 MW); HEXYLENE GLYCOL; SODIUM POLYACRYLOYLDIMETHYL TAURATE; DEHYDROXANTHAN GUM; POLYESTER-8 (1400 MW, CYANODIPHENYLPROPENOYL CAPPED); COCO-CAPRYLATE/CAPRATE; ETHYLHEXYL METHOXYCRYLENE; SIGESBECKIA ORIENTALIS WHOLE; CAFFEINE; PALMITOYL HEXAPEPTIDE-12; PALMITOYL TETRAPEPTIDE-7; ALPHA-TOCOPHEROL ACETATE; STEARYL ALCOHOL; DIPROPYLENE GLYCOL; CARBOXYPOLYMETHYLENE; LECITHIN, SOYBEAN; POLYSORBATE 20; BUTYLATED HYDROXYTOLUENE; PHENOXYETHANOL; SODIUM BENZOATE; WATER; BUTYLENE GLYCOL; BUTYLOCTYL SALICYLATE; PALMITOYL TRIPEPTIDE-1; POLYETHYLENE GLYCOL 400; PENTYLENE GLYCOL; SORBITAN SESQUIISOSTEARATE; PPG-8-CETETH-20; GLYCERYL MONOSTEARATE; EDETATE DISODIUM ANHYDROUS; POTASSIUM SORBATE; SILICON DIOXIDE; LAUROYL LYSINE; BIOSACCHARIDE GUM-1; POTASSIUM HYDROXIDE; SODIUM CITRATE

CLINIQUE SMART CLINICAL REPAIR BROAD SPECTRUM SPF 30

Active Ingredients

AVOBENZONE 3.0%
HOMOSALATE 7.0%
OCTINOXATE 3.5%
OCTISALATE 4.5%

Purpose

Sunscreen

Use

helps prevent sunburn

Warnings

For External use only

Do not use

on damaged or broken skin

When using this product

keep out of eyes. Rinse with water to remove.

Stop use and ask a doctor

if rash occurs

Keep out of reach of children.

If product is swallowed, get medical help or contact a Poison Control Center right away.

Direction

- For sunscreen use:
- apply liberally 15 minutes before sun exposure
- reapply at least every two hours
- use a water resistant sunscreen if swimming or sweating
- Sun Protection Measures. Spending time in the sun increases your risk of skin cancer and early skin aging. To decrease this risk, regularly use a sunscreen with a Broad Spectrum SPF value of 15 or higher and other sun protection measures including:
- limit time in the sun, especially from 10 a.m.–2 p.m.
- wear long-sleeved shirts, pants, hats and sunglasses
- children under 6 months of age: ask a doctor

Inactive Ingredients

water\aqua\eau, glycerin, butylene glycol, coco-caprylate/caprate, polyester-8, ethylhexyl methoxycrylene, butyloctyl salicylate, acrylates copolymer, dextrin palmitate, peg-100 stearate, silica, polyglyceryl-2 stearate, whey protein\lactis protein\protéine du petit-lait, algae extract, saccharomyces ferment, caprylyl glycol, sigesbeckia orientalis (st. paul's wort) extract, caffeine, lauroyl lysine, sodium hyaluronate, biosaccharide gum-1, 7-dehydrocholesterol, plankton extract, acetyl hexapeptide-8, palmitoyl tripeptide-1, palmitoyl hexapeptide-12, palmitoyl tetrapeptide-7, peg-8, tocopheryl acetate, pentylene glycol, hexylene glycol, sodium polyacryloyldimethyl taurate, stearyl alcohol, dehydroxanthan gum, dipropylene glycol, carbomer, potassium hydroxide, glyceryl polymethacrylate, acrylates/beheneth-25 methacrylate copolymer, lecithin, polysorbate 20, sorbitan sesquiisostearate, ppg-8-ceteth-20, glyceryl stearate, sorbeth-30 tetraisostearate, acrylates/c10-30 alkyl acrylate crosspolymer, bht, sodium citrate, disodium edta, phenoxyethanol, sodium benzoate, potassium sorbate <iln51459>

Other Information

protect the product in this container from excessive heat and direct sun

Principal Display Panel

CLINIQUE

smart clinical repair

broad spectrum SPF 30

wrinkle correcting cream

CL1870 PEPTIDE COMPLEX

POIDS NET WT. 1.7 OZ./50 ml e